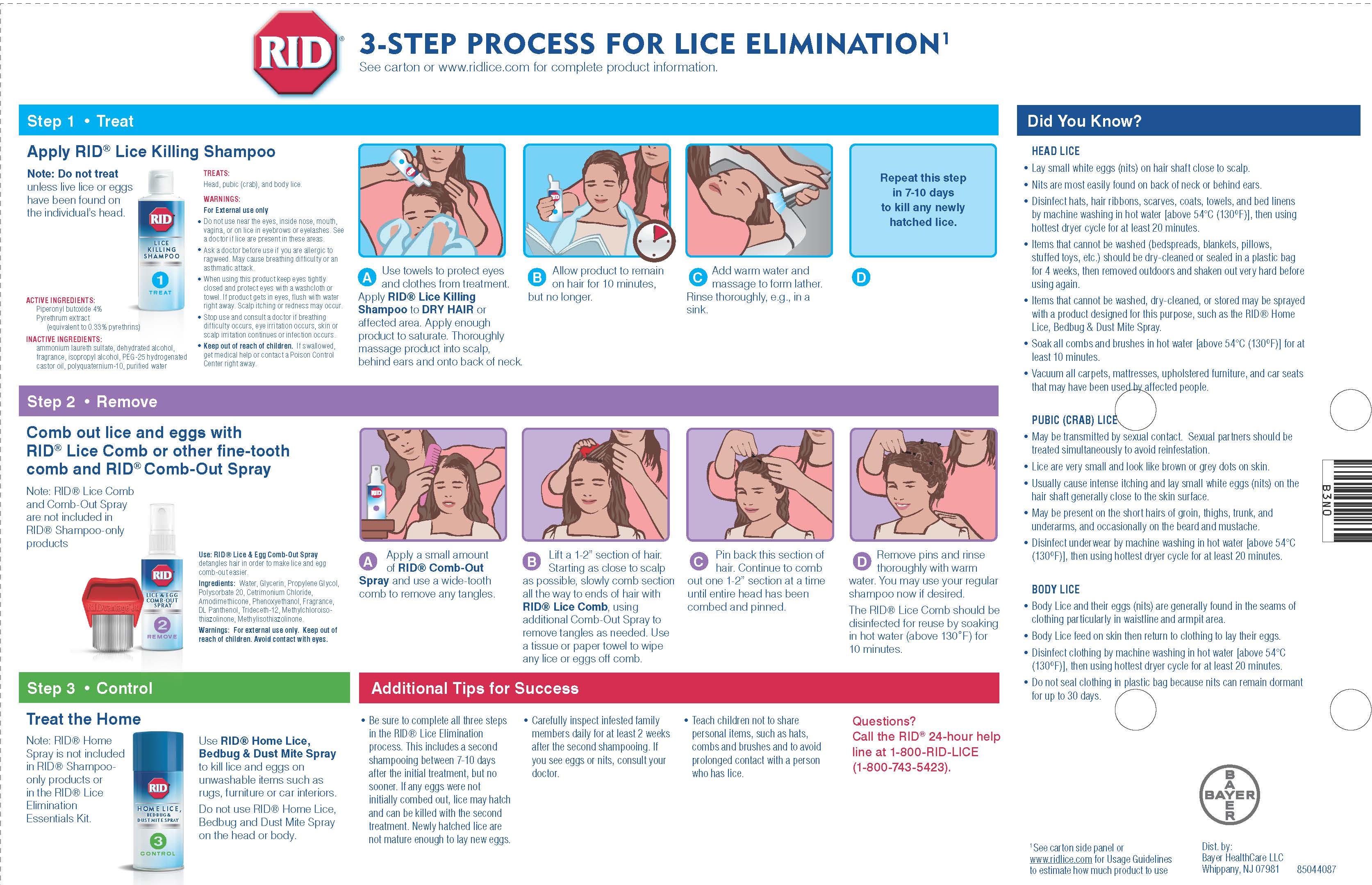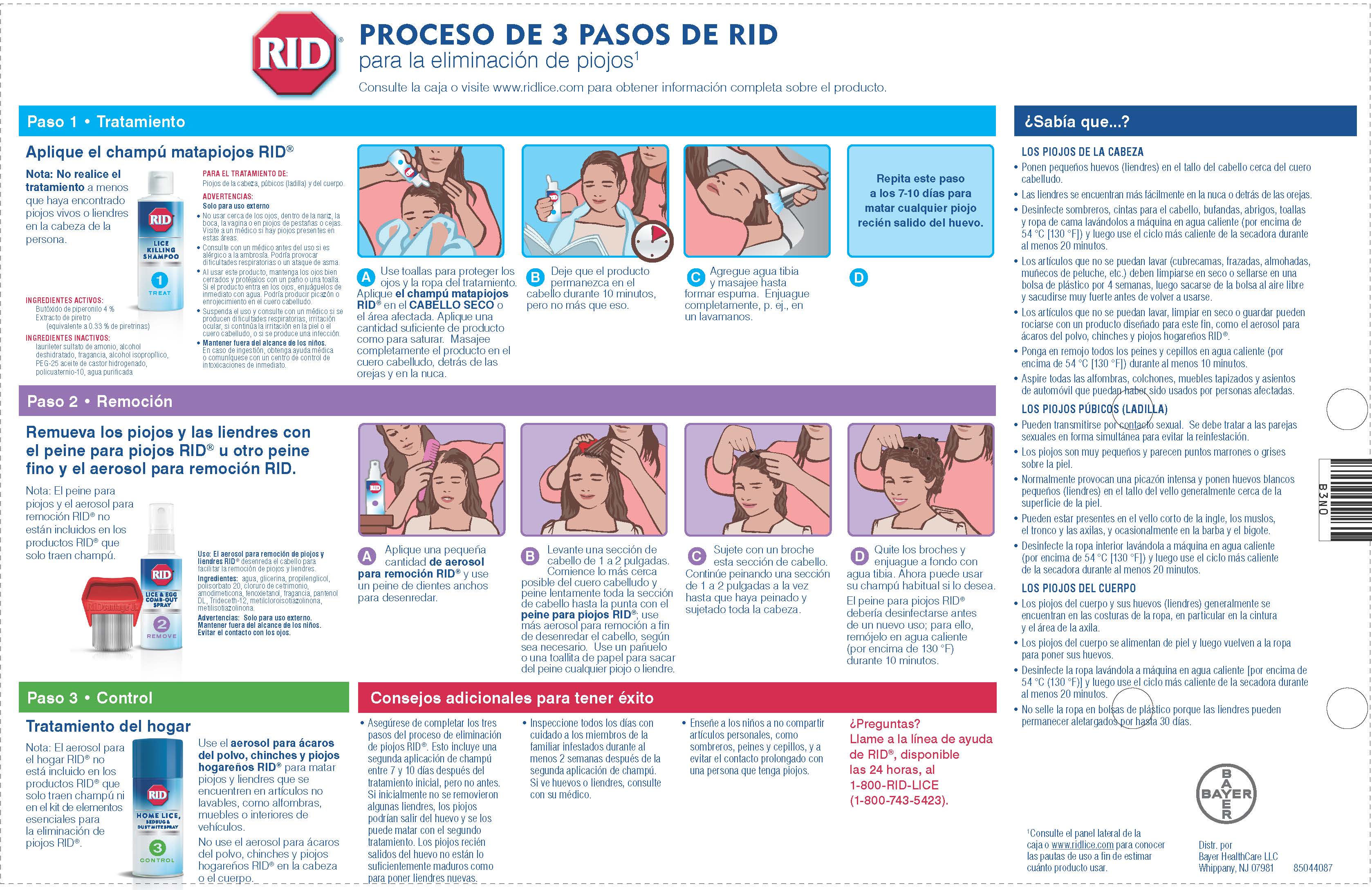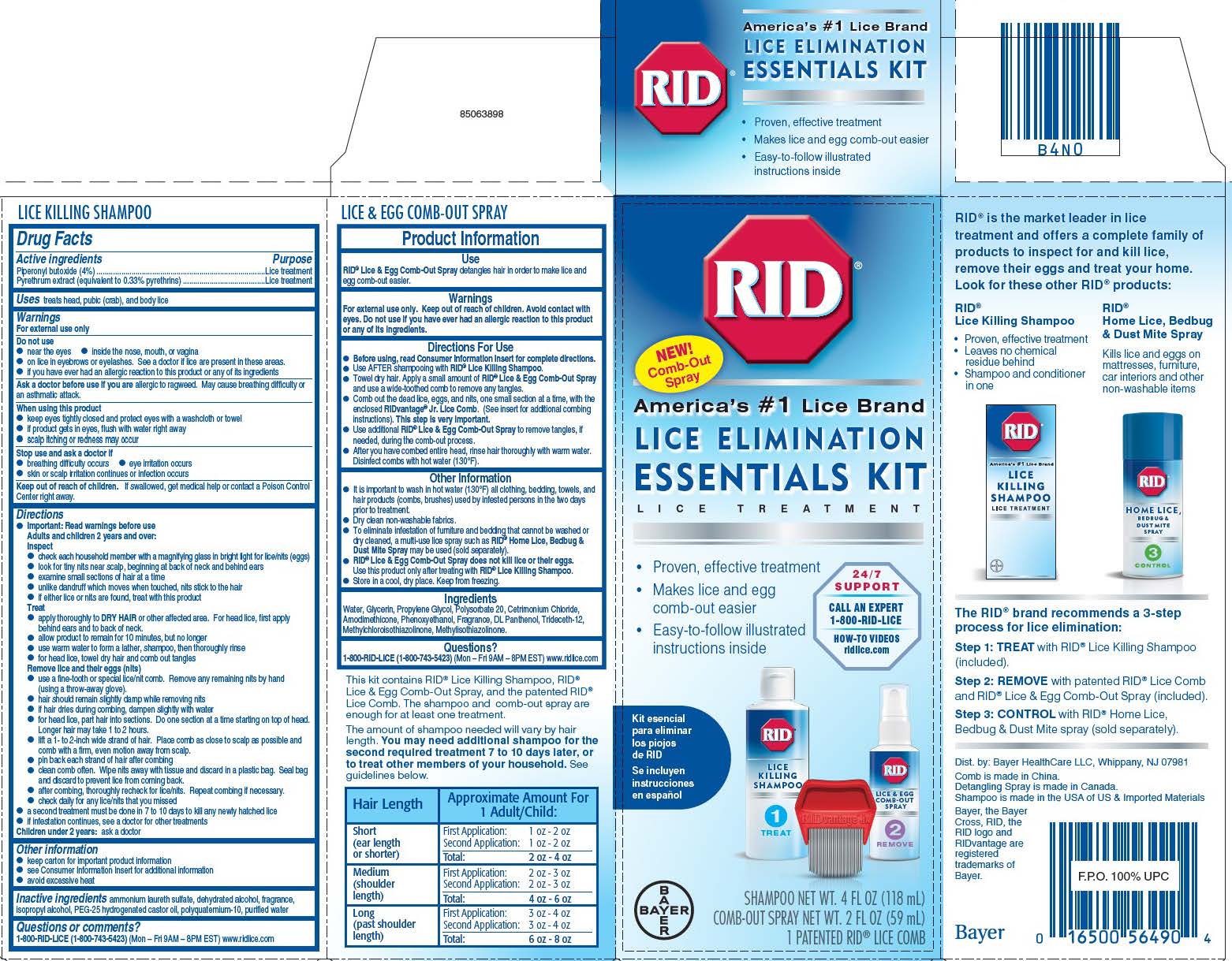 DRUG LABEL: RID Lice Elimination Essentials
NDC: 0280-9070 | Form: KIT | Route: TOPICAL
Manufacturer: Bayer HealthCare LLC.
Category: otc | Type: HUMAN OTC DRUG LABEL
Date: 20191104

ACTIVE INGREDIENTS: PYRETHRUM EXTRACT 3.3 mg/1 mL; PIPERONYL BUTOXIDE 40 mg/1 mL
INACTIVE INGREDIENTS: ALCOHOL; ISOPROPYL ALCOHOL; POLYQUATERNIUM-10 (1000 MPA.S AT 2%); AMMONIUM LAURETH-2 SULFATE; HYDROGENATED CASTOR OIL; WATER

RID Lice Elimination Essentials Kit

Drug Facts

Shampoo

Active ingredients

Piperonyl butoxide (4%)

Pyrethrum extract (equivalent to 0.33% pyrethrins)

Purpose

Lice treatment

Uses

Uses treats head, pubic (crab), and body lice

Warnings

For external Use only

Do not use

· near the eyes

· inside the nose, mouth, or vagina

· on lice in eyebrows or eyelashes. See a doctor if lice are present

in these areas.

· if you have ever had an allergic reaction to this product or any of its

ingredients

Ask a doctor before use if you are allergic to ragweed. May cause breathing difficulty or an asthmatic attack.

When using this product

● keep eyes tightly closed and protect eyes with a washcloth or

towel

● if product gets in eyes, flush with water right away

● scalp itching or redness may occur

Stop use and ask a doctor if

● breathing difficulty occurs

● eye irritation occurs

● skin or scalp irritation continues or infection occurs

Keep out of reach of children. If swallowed, get medical help or contact a Poison Control Center right away.

Directions

● Important: Read warnings before use

Adults and children 2 years and over:

Inspect

● check each household member with a magnifying glass in bright

light for lice/nits (eggs)

● look for tiny nits near scalp, beginning at back of neck and

behind ears

● examine small sections of hair at a time

● unlike dandruff which moves when touched, nits stick to the hair

● if either lice or nits are found, treat with this product

Treat

● apply thoroughly to DRY HAIR or other affected area. For head

lice, first apply behind ears and to back of neck.

● allow product to remain for 10 minutes, but no longer

● use warm water to form a lather, shampoo, then thoroughly

rinse

● for head lice, towel dry hair and comb out tangles

Remove lice and their eggs (nits)

● use a fine-tooth or special lice/nit comb. Remove any remaining

nits by hand (using a throw-away glove).

● hair should remain slightly damp while removing nits

● if hair dries during combing, dampen slightly with water

● for head lice, part hair into sections. Do one section at a time

starting on top of head. Longer hair may take 1 to 2 hours.

● lift a 1- to 2-inch wide strand of hair. Place comb as close to

scalp as possible and comb with a firm, even motion away from

scalp.

● pin back each strand of hair after combing

● clean comb often. Wipe nits away with tissue and discard in a

plastic bag. Seal bag and discard to prevent lice from coming

back.

● after combing, thoroughly recheck for lice/nits. Repeat combing

if necessary.

● check daily for any lice/nits that you missed

● a second treatment must be done in 7 to 10 days to kill any

newly hatched lice

● if infestation continues, see a doctor for other treatments

Children under 2 years: ask a doctor

Other information

● keep carton for important product information

● see Consumer Information Insert for additional information

● avoid excessive heat

INACTIVE INGREDIENT

Inactive ingredients ammonium laureth sulfate, dehydrated alcohol, fragrance, isopropyl alcohol, PEG-25 hydrogenated castor oil, polyquaternium-10, purified water

RID Lice & Egg Comb Out Spray

Use

RID® Lice & Egg Comb-Out Spray detangles hair in order to make lice and egg comb-out easier.

Warnings

For external use only. Keep out of reach of children. Avoid contact with eyes. Do not use if you have ever had an allergic reaction to this product or any of its ingredients.

Directions

Directions For Use

● Before using, read Consumer Information Insert for complete directions.

● Use AFTER shampooing with RID® Lice Killing Shampoo.

● Towel dry hair. Apply a small amount of RID® Lice & Egg Comb-Out Spray and use a wide-toothed

comb to remove any tangles.

● Comb out the dead lice, eggs, and nits, one small section at a time, with the enclosed RIDvantage® Jr.

Lice Comb. (See insert for additional combing instructions). This step is very important.

● Use additional RID® Lice & Egg Comb-Out Spray to remove tangles, if needed, during the comb-out

process.

● After you have combed entire head, rinse hair thoroughly with warm water. Disinfect combs with hot

water (130ºF).

Other Information

● It is important to wash in hot water (130ºF) all clothing, bedding, towels, and hair products (combs,

brushes) used by infested persons in the two days prior to treatment.

● Dry clean non-washable fabrics.

● To eliminate infestation of furniture and bedding that cannot be washed or dry cleaned, a multi-use lice

spray such as RID® Home Lice, Bedbug & Dust Mite Spray may be used.

● RID® Lice & Egg Comb-Out Spray does not kill lice or their eggs. Use this product only after treating

with RID® Lice Killing Shampoo.

● Store in a cool, dry place. Keep from freezing.

Ingredients

Water, Glycerin, Propylene Glycol, Polysorbate 20, Cetrimonium Chloride, Amodimethicone, Phenoxyethanol, Fragrance, DL Panthenol, Trideceth-12, Methylchloroisothiazolinone, Methylisothiazolinone.

Questions?

1-800-RID-LICE (1-800-743-5423) (Mon – Fri 9AM – 8PM EST)

Questions or comments? 1-800-RID-LICE (1-800-743-5423) (Mon – Fri 9AM – 8PM EST) www.ridlice.com